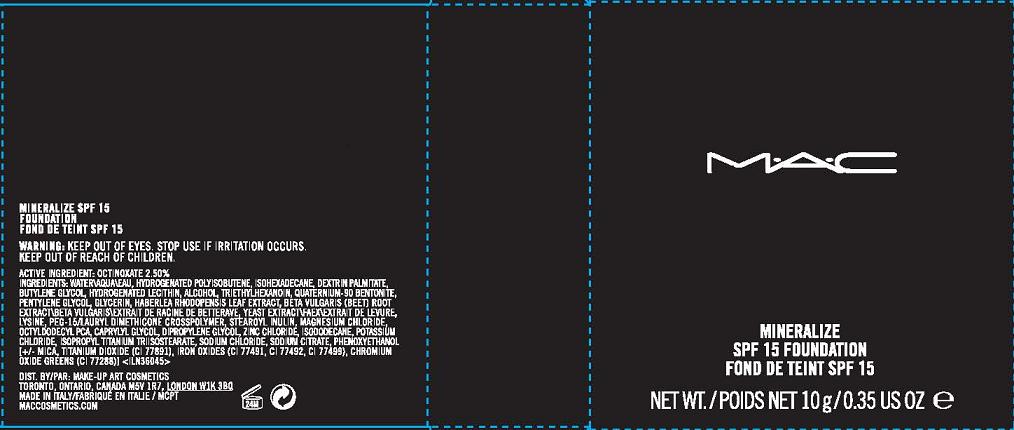 DRUG LABEL: MINERALIZE FOUNDATION
NDC: 40046-0037 | Form: CREAM
Manufacturer: MAKE-UP ART COSMETICS
Category: otc | Type: HUMAN OTC DRUG LABEL
Date: 20100518

ACTIVE INGREDIENTS: OCTINOXATE 10 g/100 g

ACTIVE INGREDIENT: OCTINOXATE 2.5%

WARNINGS

WARNING: KEEP OUT OF EYES. STOP USE IF IRRITATION OCCURS. KEEP OUT OF REACH OF CHILDREN.

PACKAGE LABEL

PRINCIPAL DISPLAY PANEL:

MAC

MINERALIZE

SPF 15 FOUNDATION

NET WT./POIDS NET 10g/0.35 US OZ

DIST. BY MAKE-UP ART COSMETICS

TORONTO, ONTARIO, CANADA M5V 1R7